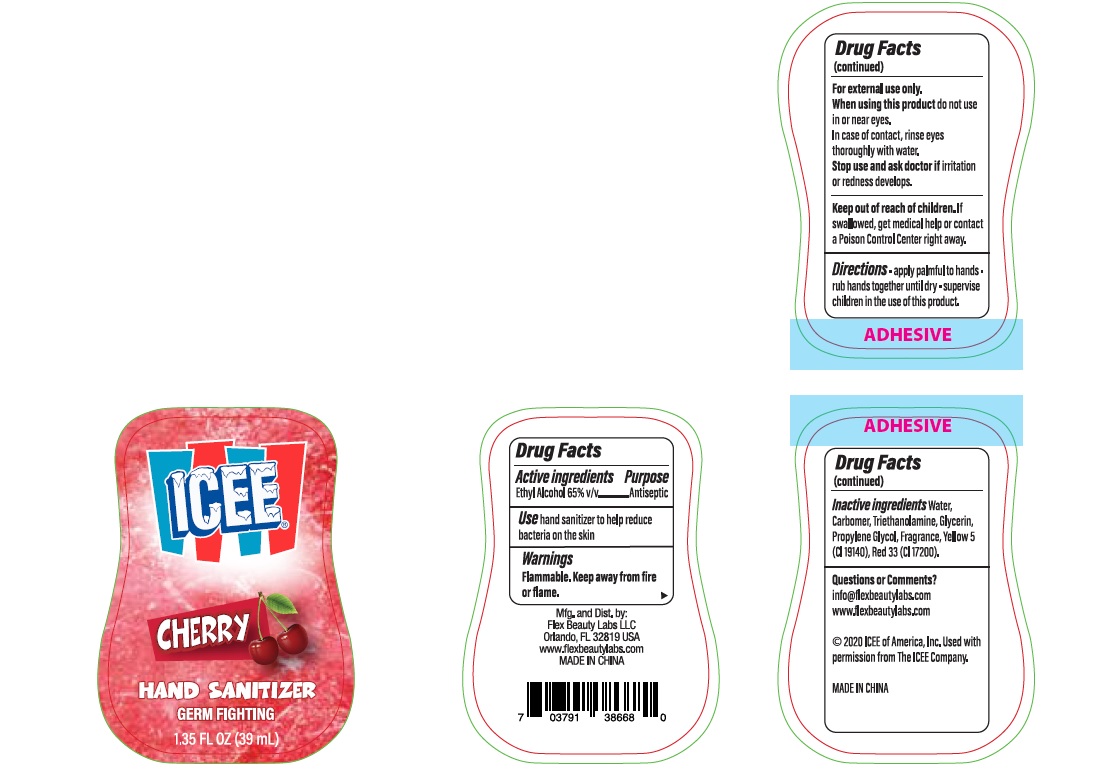 DRUG LABEL: Icee Hand Sanitizer
NDC: 72308-022 | Form: GEL
Manufacturer: Flex Beauty Labs
Category: otc | Type: HUMAN OTC DRUG LABEL
Date: 20200804

ACTIVE INGREDIENTS: ALCOHOL 0.65 mL/1 mL
INACTIVE INGREDIENTS: WATER; TROLAMINE; CARBOMER HOMOPOLYMER, UNSPECIFIED TYPE; PROPYLENE GLYCOL; GLYCERIN; D&C RED NO. 33; FD&C YELLOW NO. 5

Icee Cherry Hand Sanitizer

Active Ingredients

Ethyl Alcohol 65%.................Antiseptic

Purpose

Antiseptic

Use

hand sanitizer to help reduce bacteria on the skin

Safety Instructions

Flammable, Keep away from fire and flame

When using this product

In case of contact,rinse eyes thoroughly with water.

Do not use in or near eyes.

KEEP OUT OF REACH OF CHILDREN

If swallowed, get medical help or contact Poison Control center right away.

Inactive Ingredients

Water (aqua), Triethanolamine, Carbomer, Fragrance, Glycerin. Propylene Glycol, Red 33,Yellow 5.

Directions

- apply palmful to hands.
- rub hands together vigorously until dry.
- supervise children in the use of this product.